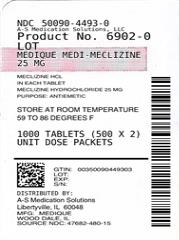 DRUG LABEL: Medique Medi-Meclizine
NDC: 50090-4493 | Form: TABLET
Manufacturer: A-S Medication Solutions
Category: otc | Type: HUMAN OTC DRUG LABEL
Date: 20210415

ACTIVE INGREDIENTS: MECLIZINE HYDROCHLORIDE 25 mg/1 1
INACTIVE INGREDIENTS: ANHYDROUS LACTOSE; SILICON DIOXIDE; STARCH, CORN; D&C YELLOW NO. 10; MAGNESIUM STEARATE; MICROCRYSTALLINE CELLULOSE; SODIUM STARCH GLYCOLATE TYPE A POTATO

Drug Facts

Active ingredient (in each tablet)

Meclizine Hydrochloride 25 mg

Purpose

Antiemetic

Uses

For the prevention and treatment of the nausea, vomiting, or dizziness associated with motion sickness.

Warnings

Do not use

- for children under 12 years of age unless directed by a doctor
- for frequent or prolonged use except under the advice of a doctor

Ask a doctor before use if you have

- breathing problems such as emphysema or chronic bronchitis
- glaucoma
- difficulty in urination due to enlargement of the prostate gland

if you are

- taking sedatives or tranquilizers

When using this product

- drowsiness may occur
- alcohol, sedatives and tranquilizers may increase the drowsiness effect
- avoid alcoholic beverages while taking this product
- use caution when driving a motor vehicle or operating machinery

Do not exceed recommended dosage.

PREGNANCY OR BREAST FEEDING

If pregnant or breast-feeding, ask a health professional before use.

Keep out of reach of children. In case of overdose, get medical help or contact a Poison Control Center right away.

Directions

- do not use more than directed
- to prevent motion sickness, take the first dose one hour before starting activity

Adults and children: (12 years and older) 1 to 2 tablets once daily or as directed by a doctor. Do not exceed 2 tablets in 24 hours.

Children under 12 years: Do not give to children under 12 years of age.

Other information

- store at room temperature 59- 86º F (15-30ºC)
- tamper-evident sealed packets
- do not use any opened or torn packets

Inactive ingredients

anhydrous lactose, colloidal silicon dioxide, corn starch, D&C yellow # 10, magnesium stearate, microcrystalline cellulose, sodium starch glycolate

Questions or comments?

1-800-634-7680

HOW SUPPLIED

Product: 50090-4493

NDC: 50090-4493-0 2 TABLET in a PACKET / 500 in a BOX